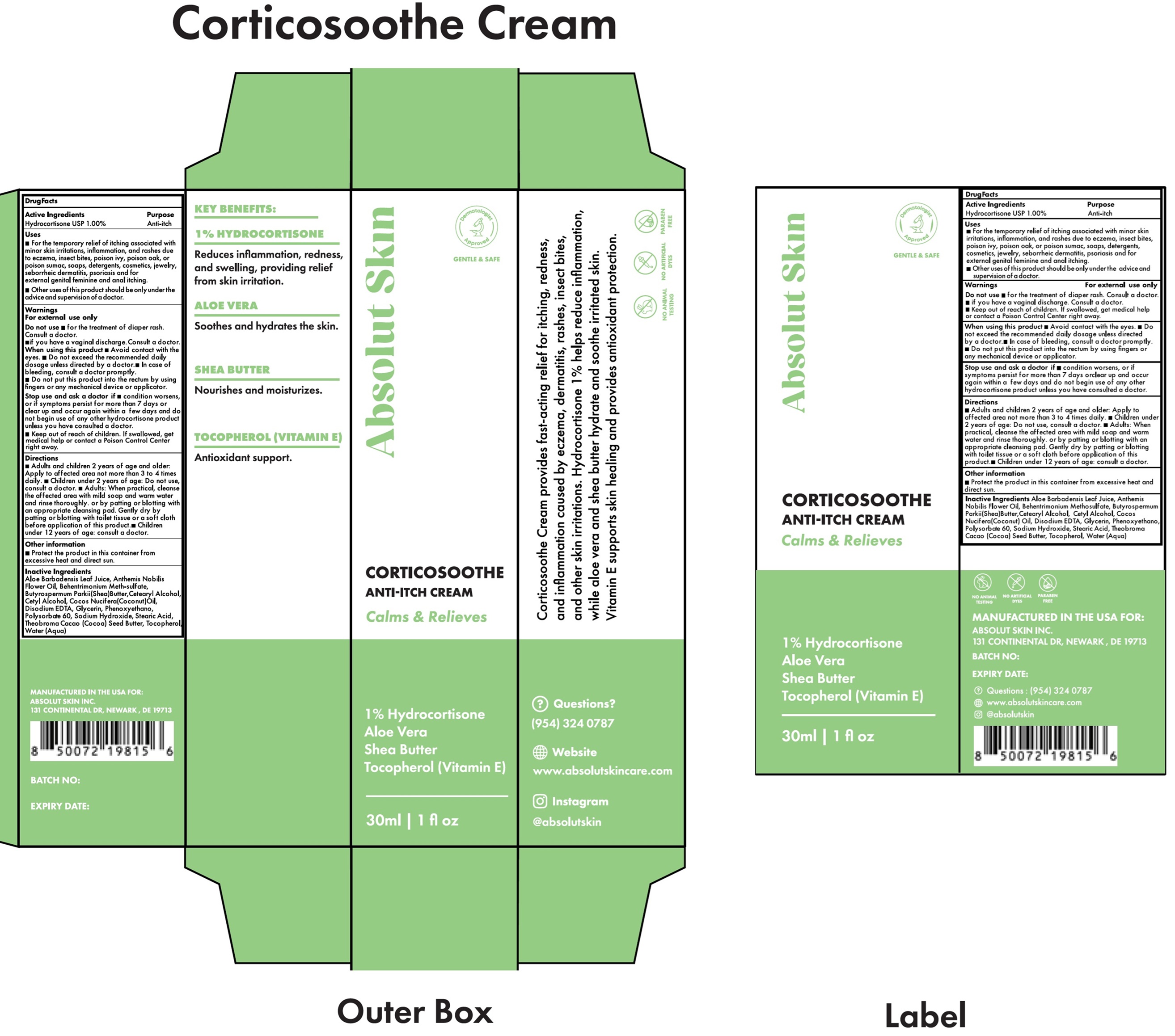 DRUG LABEL: Absolut Skin Corticosoothe Anti-Itch
NDC: 87184-899 | Form: CREAM
Manufacturer: Absolut Skin Incorporated
Category: otc | Type: HUMAN OTC DRUG LABEL
Date: 20251119

ACTIVE INGREDIENTS: HYDROCORTISONE 10 mg/1 mL
INACTIVE INGREDIENTS: ALOE VERA LEAF JUICE; CHAMAEMELUM NOBILE FLOWER OIL; BEHENTRIMONIUM METHOSULFATE; SHEA BUTTER; CETOSTEARYL ALCOHOL; CETYL ALCOHOL; COCONUT OIL; EDETATE DISODIUM; GLYCERIN; PHENOXYETHANOL; POLYSORBATE 60; SODIUM HYDROXIDE; STEARIC ACID; COCOA BUTTER; TOCOPHEROL; WATER

Absolut Skin Corticosoothe Anti-Itch Cream

Active Ingredients

Hydrocortisone USP I .00%

Purpose

Anti-itch

Uses:

• For the temporary relief of itching associated with minor skin irritations, inflammation, and rashes due to eczema, insect bites, poison ivy, poison oak, or poison sumac, soaps, detergents, cosmetics, jewelry, seborrheic dermatitis, psoriasis and for external genital feminine and anal itching.
• Other uses of this product should be only under the advice and supervision of a doctor.

Warnings

For external use only

Do not use

• for the treatment of diaper rash. Consult a doctor.

• if you have a vaginal discharge. Consult a doctor.

When using this product

• Avoid contact with the eyes. • Do not exceed the recommended daily dosage unless directed by a doctor.• In case of bleeding, consult a doctor promptly. • Do not put this product into the rectum by using fingers or any mechanical device or applicator.

Stop use and ask a doctor if

• condition worsens, or if symptoms persist for more than 7 days or clear up and occur again within a few days and do not begin use of any other hydrocortisone product unless you have consulted a doctor.

Keep out of reach of children.

If swallowed, get medical help or contact a Poison Control Center right away.

Directions

• Adults and children 2 years of age and older: Apply to affected area not more than 3 to 4 times daily. • Children under 2 years of age: Do not use, consult a doctor. • Adults: When practical, cleanse the affected area with mild soap and warm water and rinse thoroughly. or by patting or blotting with an appropriate cleansing pad. Gently dry by patting or blotting with toilet tissue or a soft cloth before application of this product.• Children under 12 years of age: consult a doctor.

Other Information

- Protect the product in this container from excessive heat and direct sun.

Inactive Ingredients

Aloe Barbadensis Leaf Juice, Anthemis Nobilis Flower Oil, Behentrimonium Methosulfate, Butyrospermum Parkii(Shea)Butter,Cetearyl Alcohol, Cetyl Alcohol, Cocos Nucifera(Coconut) Oil, Disodium EDTA, Glycerin, Phenoxyethanol, Polysorbate 60, Sodium Hydroxide, Stearic Acid, Theobroma Cacao (Cocoa) Seed Butter, Tocopherol, Water (Aqua)